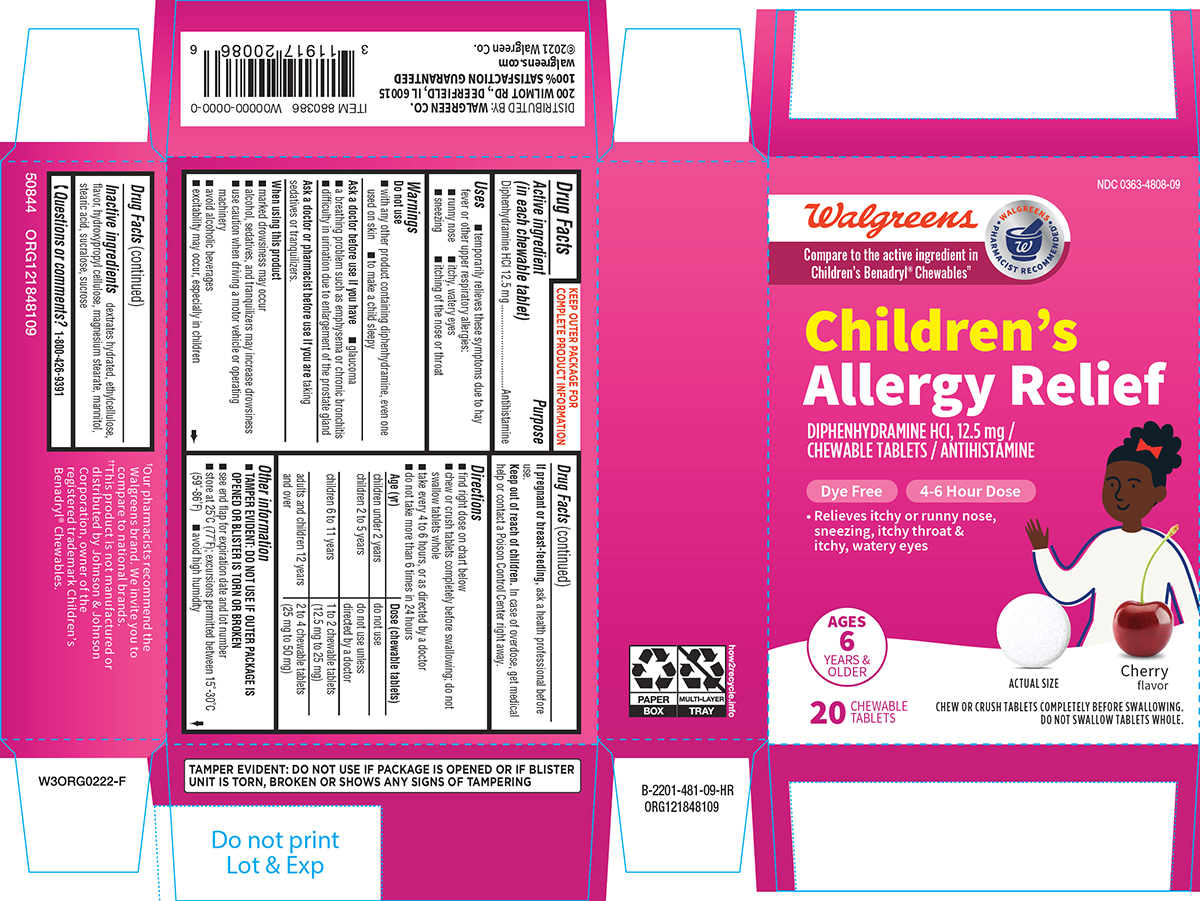 DRUG LABEL: Childrens Allergy Relief
NDC: 0363-4808 | Form: TABLET, CHEWABLE
Manufacturer: Walgreen Company
Category: otc | Type: HUMAN OTC DRUG LABEL
Date: 20250510

ACTIVE INGREDIENTS: DIPHENHYDRAMINE HYDROCHLORIDE 12.5 mg/1 1
INACTIVE INGREDIENTS: DEXTROSE MONOHYDRATE; ETHYLCELLULOSE, UNSPECIFIED; HYDROXYPROPYL CELLULOSE, UNSPECIFIED; MAGNESIUM STEARATE; MANNITOL; STEARIC ACID; SUCRALOSE; SUCROSE

Walgreens 44-481-Childrens Allergy Relief

Active ingredient (in each chewable tablet)

Diphenhydramine HCl 12.5 mg

Purpose

Antihistamine

Uses

- temporarily relieves these symptoms due to hay fever or other upper respiratory allergies:
  - runny nose
  - itchy, watery eyes
  - sneezing
  - itching of the nose or throat

Warnings

Do not use

- with any other product containing diphenhydramine, even one used on skin
- to make a child sleepy

Ask a doctor before use if you have

- glaucoma
- a breathing problem such as emphysema or chronic bronchitis
- difficulty in urination due to enlargement of the prostate gland

Ask a doctor or pharmacist before use if you are

taking sedatives or tranquilizers.

When using this product

- marked drowsiness may occur
- alcohol, sedatives, and tranquilizers may increase drowsiness
- use caution when driving a motor vehicle or operating machinery
- avoid alcoholic beverages
- excitability may occur, especially in children

If pregnant or breast-feeding,

ask a health professional before use.

Keep out of reach of children.

In case of overdose, get medical help or contact a Poison Control Center right away.

Directions

- find right dose on chart below
- chew or crush tablets completely before swallowing; do not swallow tablets whole
- take every 4 to 6 hours, or as directed by a doctor
- do not take more than 6 times in 24 hours

Age (yr) | Dose (chewable tablets)
children under 2 years | do not use
children 2 to 5 years | do not use unless directed by a doctor
children 6 to 11 years | 1 to 2 chewable tablets (12.5 mg to 25 mg)
adults and children 12 years and over | 2 to 4 chewable tablets (25 mg to 50 mg)

Other information

- TAMPER EVIDENT: DO NOT USE IF OUTER PACKAGE IS OPENED OR BLISTER IS TORN OR BROKEN
- see end flap for expiration date and lot number
- store at 25°C (77°F); excursions permitted between 15°-30°C (59°-86°F)
- avoid high humidity

Inactive ingredients

dextrates hydrated, ethylcellulose, flavor, hydroxypropyl cellulose, magnesium stearate, mannitol, stearic acid, sucralose, sucrose

Questions or comments?

1-800-426-9391

Principal display panel

NDC 0363-4808-09

Walgreens

Compare to the active ingredient in
Children’s Benadryl® Chewables††

WALGREENS PHARMACIST RECOMMENDED†

Children’s
Allergy Relief

DIPHENHYDRAMINE HCl, 12.5 mg /
CHEWABLE TABLETS / ANTIHISTAMINE

Dye Free 4-6 Hour Dose

• Relieves itchy or runny nose,
sneezing, itchy throat &
itchy, watery eyes

AGES
6
YEARS &
OLDER

ACTUAL SIZE

Cherry
flavor

20 CHEWABLE
TABLETS

CHEW OR CRUSH TABLETS COMPLETELY BEFORE SWALLOWING.
DO NOT SWALLOW TABLETS WHOLE.

TAMPER EVIDENT: DO NOT USE IF PACKAGE IS OPENED OR IF BLISTER
UNIT IS TORN, BROKEN OR SHOWS ANY SIGNS OF TAMPERING

†Our pharmacists recommend the
Walgreens brand. We invite you to
compare to national brands.
††This product is not manufactured or
distributed by Johnson & Johnson
Corporation, owner of the
registered trademark Children’s
Benadryl® Chewables.

DISTRIBUTED BY: WALGREEN CO.
200 WILMOT RD., DEERFIELD, IL 60015
100% SATISFACTION GUARANTEED
walgreens.com
©2021 Walgreen Co.

50844 ORG121848009

Walgreens 44-481